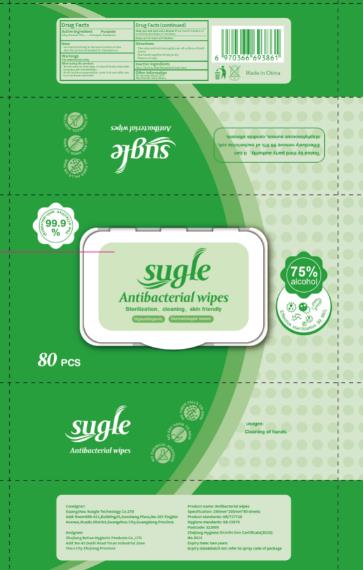 DRUG LABEL: Wet Wipe
NDC: 76906-006 | Form: CLOTH
Manufacturer: Zhejiang BeiTao Hygienic Products Co., Ltd.
Category: otc | Type: HUMAN OTC DRUG LABEL
Date: 20241222

ACTIVE INGREDIENTS: ALCOHOL 75 g/100 mL
INACTIVE INGREDIENTS: WATER; ALOE VERA LEAF; GLYCERIN

76906-006 wet wipes 75% Alcohol

Active Ingredient

Ethyl Alcohol 75%

Purpose

Antiseptice Handwash

USE

For hand sanitizing to decrease bacteria on the skin.
Do not recommended for repeated use.

Warning

For external use only
When using this product,

Do not use in or near eyes. In case of touch, rinse with running water immediately.

Avoid moisture evaporation, cover it at once after use.

Can not throw into toilet
Stop use and ask a doctor if too much irritation or sensitivity develops or increases.

Keep out of reach of children.

Directions

Take wipe and rub thoroughly over all surfaces of both hands

Rub hands together briskly to dry

Dispose of Wipe

Inactive ingredients

Aqua,Glycerin,Aloe Barbadensis Leaf Juice.

Other Information

Do not store above 110F

May discolor some fabrics

PACKAGE LABEL

80PCS NDC 76906-006-01